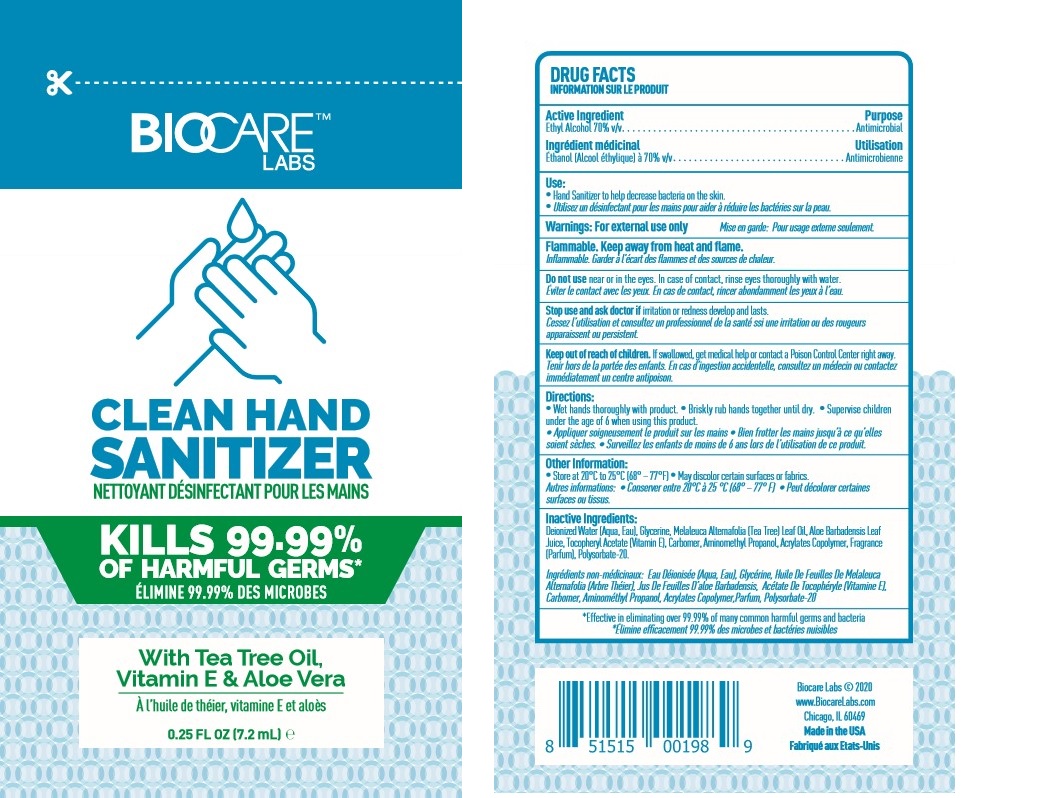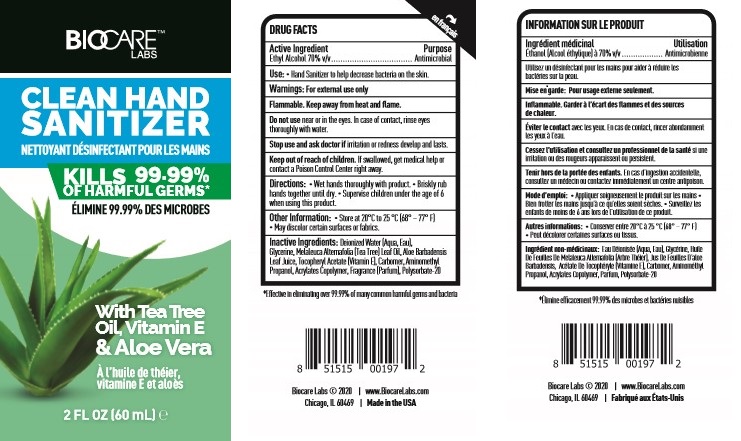 DRUG LABEL: BIOCARE LABS CLEAN HAND SANITIZER
NDC: 54602-100 | Form: GEL
Manufacturer: BIOCARE LABS INC.
Category: otc | Type: HUMAN OTC DRUG LABEL
Date: 20201005

ACTIVE INGREDIENTS: ALCOHOL .7 L/1 L
INACTIVE INGREDIENTS: WATER; GLYCERIN; MELALEUCA ALTERNIFOLIA LEAF; ALOE VERA LEAF; .ALPHA.-TOCOPHEROL ACETATE; CARBOMER 940; AMINOMETHYLPROPANOL; BUTYL ACRYLATE/METHYL METHACRYLATE/METHACRYLIC ACID COPOLYMER (18000 MW); FRAGRANCE LEMON ORC2001060; POLYSORBATE 20

BIOCARE LABS CLEAN HAND SANITIZER

DRUG FACTS

Active Ingredient

Ethyl Alcohol 70% v/v

Uses:

Hand Sanitizer to help decrease bacteria on the skin.

Warnings:

For external use only.

Flammable. Keep away from heat or flame.

KEEP OUT OF REACH OF CHILDREN SECTION

If swallowed, get medical help or contact a Poison Control Center right away.

Do not use:

near or in the eyes. In case of contact, rinse eyes thoroughly with water.

Keep out of reach of children. If swallowed, get medical help or contact a Poison Control Center right away.

Stop use and ask a doctor if: if irritation or redness develop and lasts.

Directions:

• Wet hands thoroughly with product.

• Briskly rub hands together until dry.

• Supervise children under the age of 6 when using this product

Inactive Ingredients:

Deionized Water (Aqua, Eau), Glycerine, Melaleuca Alternafolia (Tea Tree) Leaf Oil,

Aloe Barbadensis Leaf Juice, Tocopheryl Acetate (Vitamin E), Carbomer, Aminomethyl
Propanol, Acrylates Copolymer, Fragrance (Parfum), Polysorbate-20

Other Information:

• Store at 20°C to 25 °C (68° – 77° F)
• May discolor certain surfaces or fabrics.

For Questions:

Biocare Labs © 2020 Chicago, IL 60469

www.BiocareLabs.com